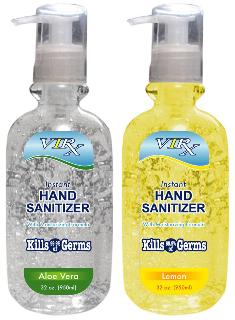 DRUG LABEL: Virx
NDC: 40104-703 | Form: GEL
Manufacturer: Ningbo Pulisi Daily Chemical Products Co., Ltd
Category: otc | Type: HUMAN OTC DRUG LABEL
Date: 20100225

ACTIVE INGREDIENTS: Alcohol 618.1 mL/947 mL
INACTIVE INGREDIENTS: Water; Glycerin; Isopropyl Myristate; Propylene Glycol; ALPHA-TOCOPHEROL ACETATE

Virx Instant Hand Sanitizer Drug Facts

WARNINGS

- For external use only * Flammable * Keep away from fire or flame
- Do not store above 40 degrees Celcius (105 degrees Fahrenheit)
- Do not use in mouth, ears and eyes
- When using this product, avoid contact with eyes
- In case of contact, flush eyes with water

INACTIVE INGREDIENT

Deionized Water, Glycerin, Isopropyl Myristate, Propylene Glycol, Tocopheryl Acetate, Aminomethyl Propanol, Carbomer, Fragrance.

ACTIVE INGREDIENT

Ethyl Alcohol 62%......................................................................................Antiseptic

Keep out of reach of children. Children must be supervised when using this product.

PURPOSE

Uses Hand Sanitizer to help decrease bacteria on the skin.

PACKAGE LABEL

MM1

Stop use and seek a doctor if redness or irritation develops and persists for more than 72 hours.

Directions:

- Pump as needed into your palms and thoroughly spread on both hands
- Rub into skin until dry